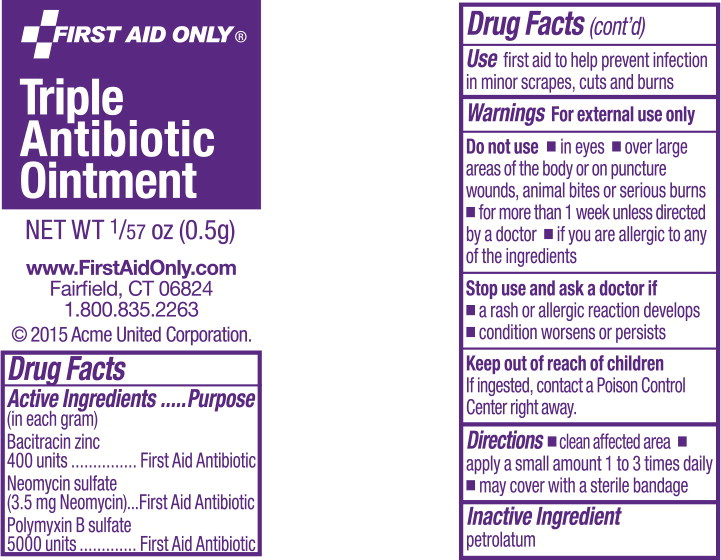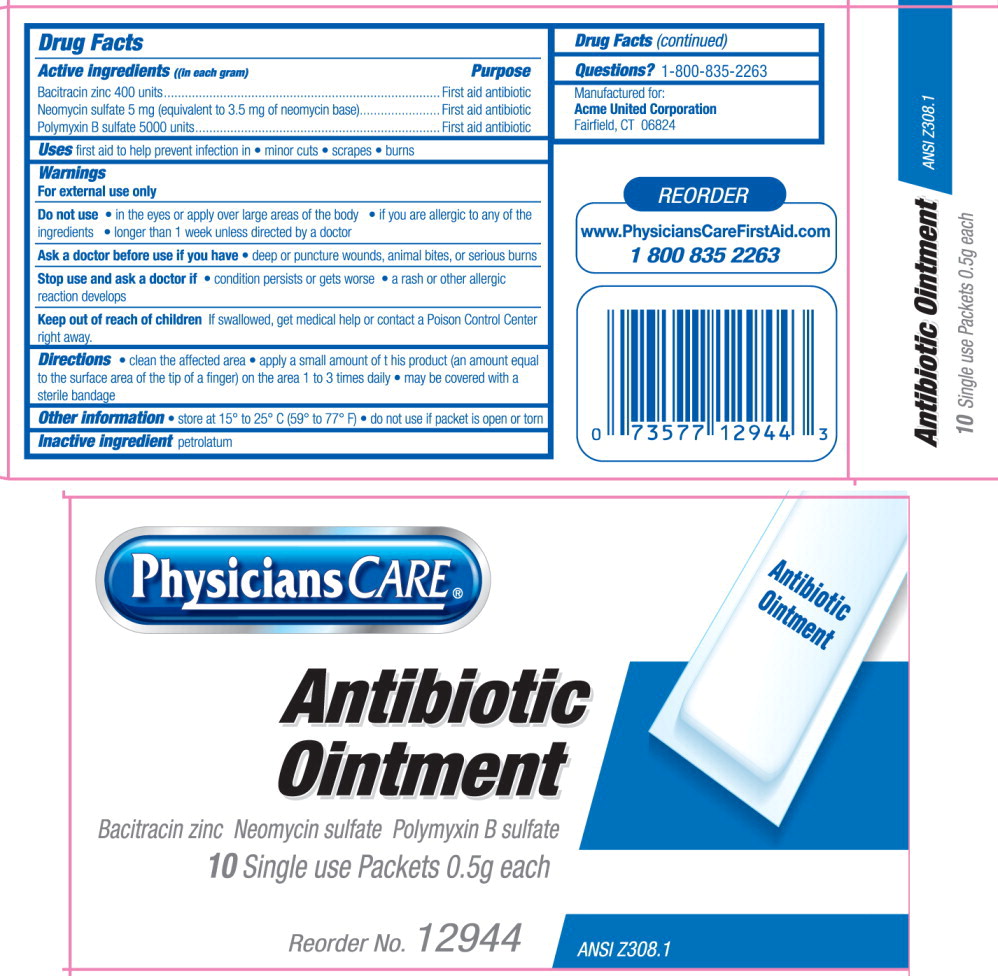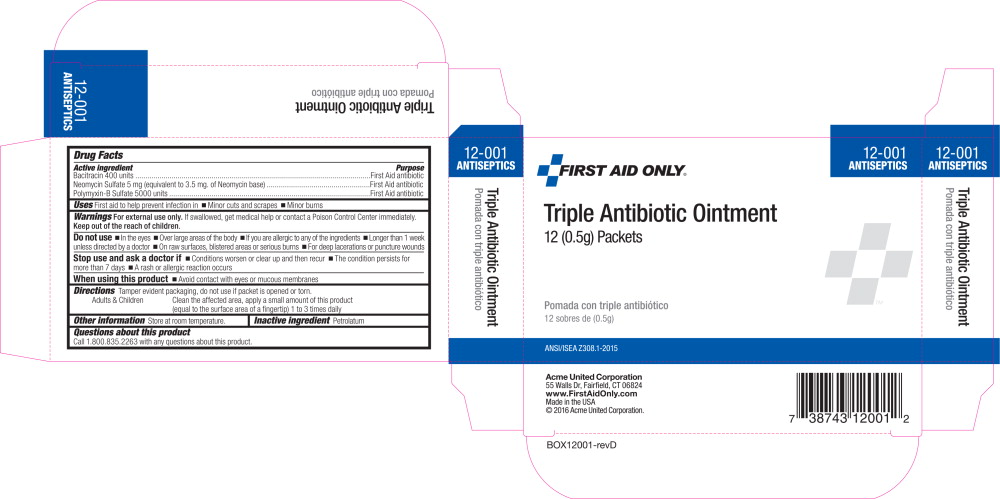 DRUG LABEL: triple antibiotic
NDC: 0924-5603 | Form: OINTMENT
Manufacturer: Acme United Corporation
Category: otc | Type: HUMAN OTC DRUG LABEL
Date: 20160309

ACTIVE INGREDIENTS: bacitracin zinc 400 [iU]/1 g; neomycin sulfate 3.5 mg/1 g; polymyxin b sulfate 5000 [iU]/1 g
INACTIVE INGREDIENTS: petrolatum

Drug Facts

Active Ingredients (in each gram)

Bacitracin zinc 400 units

Neomycin sulfate 5 mg (equivalent to 3.5 mg of neomycin base)

Polymyxin-B sulfate 5000 units

Purpose

First Aid Antibiotics

Uses

first aid to help prevent infection in

- minor cuts
- scrapes
- burns

Warnings:

For external use only.

Do not use

- in the eyes or apply over large areas of the body
- if you are allergic to any of the ingredients
- longer than 1 week unless directed by a doctor

Ask a doctor before use if you have

- deep or puncture wounds, animal bites, or serious burns

Stop use and ask a doctor if

- condition persists or gets worse
- A rash or other allergic reaction develops

KEEP OUT OF REACH OF CHILDREN

Keep out of the reach of children If swallowed, get medical help or contact a Poison Control Center right away.

Directions:

- clean the affected area
- apply a small amount of this product (an amount equal to the surface area of a finger) on the area 1 to 3 times daily
- may be covered with a sterile bandage

Other information

- Store at 15° to 25° C (59° to 77° F)
- Do not use if packet is open or torn

Inactive ingredient

Petrolatum

Questions? 1-800-835-2263

Manufactured for:
Acme United Corporation
Fairfield, CT 06824

REORDER
www.PhysiciansCareFirstAid.com
1 800 835 2263

Principal Display Panel - Packet Label

FIRST AID ONLY®

Triple
Antibiotic

Ointment

NET WT 1/57 oz (0.5g)

www.FirstAidOnly.com

Fairfield, CT 06824

1.800.835.2263

© 2015 Acme United Corporation.

PRINCIPAL DISPLAY PANEL – 10 count box

PhysiciansCARE

Antibiotic
Ointment

Bacitracin zinc Neomycin sulfate Polymyxin B sulfate
10 Single use Packets 0.5g each

Reorder No. 12944

ANSI Z308.1

PRINCIPAL DISPLAY PANEL – 12 count box

12-001
ANTISEPTICS

FIRST AID ONLY®

Triple Antibiotic Ointment

12 (0.5g) Packets

Pomada con triple antibiótico

12 sobres de (0.5g)